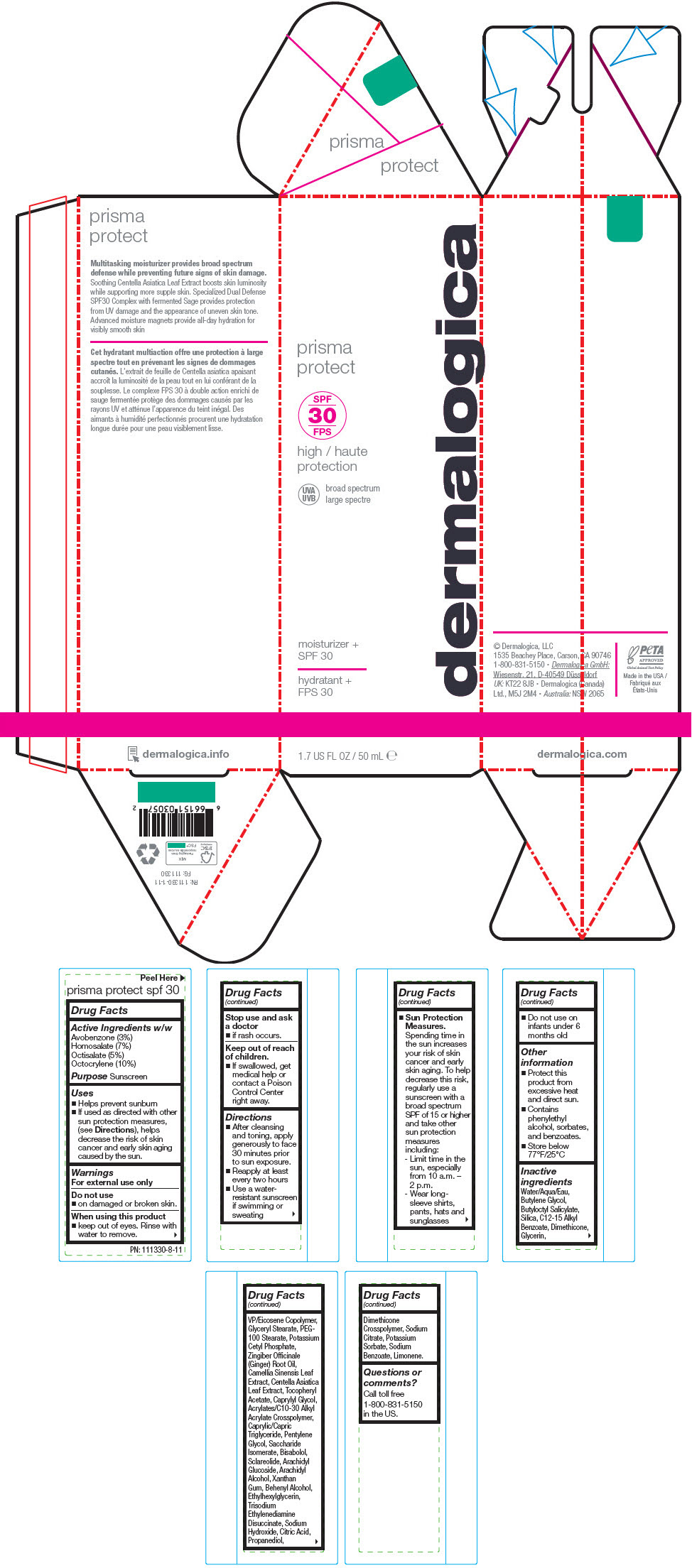 DRUG LABEL: PRISMA PROTECT SPF30
NDC: 68479-852 | Form: LOTION
Manufacturer: Dermalogica, LLC.
Category: otc | Type: HUMAN OTC DRUG LABEL
Date: 20240425

ACTIVE INGREDIENTS: Octocrylene 10 g/100 mL; Homosalate 7 g/100 mL; Octisalate 5 g/100 mL; Avobenzone 3 g/100 mL
INACTIVE INGREDIENTS: Water; Butylene Glycol; Butyloctyl Salicylate; SILICON DIOXIDE; ALKYL (C12-15) BENZOATE; Dimethicone; Glycerin; VINYLPYRROLIDONE/EICOSENE COPOLYMER; GLYCERYL MONOSTEARATE; PEG-100 Stearate; Potassium Cetyl Phosphate; Pentylene Glycol; Propanediol; Arachidyl Alcohol; Saccharide Isomerate; Caprylyl Glycol; DOCOSANOL; MEDIUM-CHAIN TRIGLYCERIDES; LEVOMENOL; Sclareolide; Xanthan Gum; Arachidyl Glucoside; Ethylhexylglycerin; .ALPHA.-TOCOPHEROL ACETATE; Trisodium Ethylenediamine Disuccinate; GINGER OIL; CENTELLA ASIATICA LEAF; Sodium Hydroxide; GREEN TEA LEAF; CITRIC ACID MONOHYDRATE; SODIUM CITRATE, UNSPECIFIED FORM; Potassium Sorbate; Sodium Benzoate

PRISMA PROTECT SPF30

Drug Facts

Active Ingredients w/w

Avobenzone (3%)
Homosalate (7%)
Octisalate (5%)
Octocrylene (10%)

Purpose

Sunscreen

Uses

- Helps prevent sunburn
- If used as directed with other sun protection measures, (see Directions), helps decrease the risk of skin cancer and early skin aging caused by the sun.

Warnings

For external use only

Do not use

- on damaged or broken skin.

When using this product

- keep out of eyes. Rinse with water to remove.

Stop use and ask a doctor

- if rash occurs.

Keep out of reach of children.

- If swallowed, get medical help or contact a Poison Control Center right away.

Directions

- After cleansing and toning, apply generously to face 30 minutes prior to sun exposure.
- Reapply at least every two hours
- Use a water-resistant sunscreen if swimming or sweating
- Sun Protection Measures. Spending time in the sun increases your risk of skin cancer and early skin aging. To help decrease this risk, regularly use a sunscreen with a broad spectrum SPF of 15 or higher and take other sun protection measures including:
  - Limit time in the sun, especially from 10 a.m. – 2 p.m.
  - Wear long-sleeve shirts, pants, hats and sunglasses
- Do not use on infants under 6 months old

Other information

- Protect this product from excessive heat and direct sun.
- Contains phenylethyl alcohol, sorbates, and benzoates.
- Store below 77°F/25°C

Inactive ingredients

Water/Aqua/Eau, Butylene Glycol, Butyloctyl Salicylate, Silica, C12-15 Alkyl Benzoate, Dimethicone, Glycerin, VP/Eicosene Copolymer, Glyceryl Stearate, PEG-100 Stearate, Potassium Cetyl Phosphate, Zingiber Officinale (Ginger) Root Oil, Camellia Sinensis Leaf Extract, Centella Asiatica Leaf Extract, Tocopheryl Acetate, Caprylyl Glycol, Acrylates/C10-30 Alkyl Acrylate Crosspolymer, Caprylic/Capric Triglyceride, Pentylene Glycol, Saccharide Isomerate, Bisabolol, Sclareolide, Arachidyl Glucoside, Arachidyl Alcohol, Xanthan Gum, Behenyl Alcohol, Ethylhexylglycerin, Trisodium Ethylenediamine Disuccinate, Sodium Hydroxide, Citric Acid, Propanediol, Dimethicone Crosspolymer, Sodium Citrate, Potassium Sorbate, Sodium Benzoate, Limonene.

Questions or comments?

Call toll free 1-800-831-5150 in the US.

PRINCIPAL DISPLAY PANEL - 50 mL Tube Carton

prisma
protect

dermalogica

SPF
30

high
protection

UVA
UVB

broad spectrum

moisturizer +
SPF 30

1.7 US FL OZ / 50 mL ℮